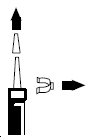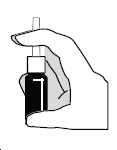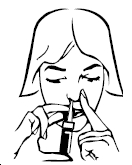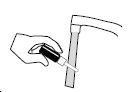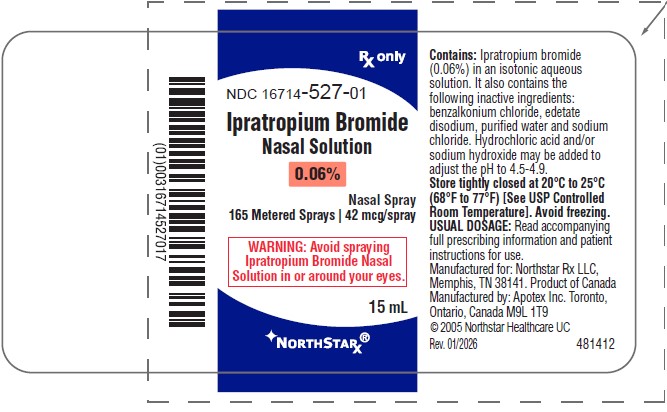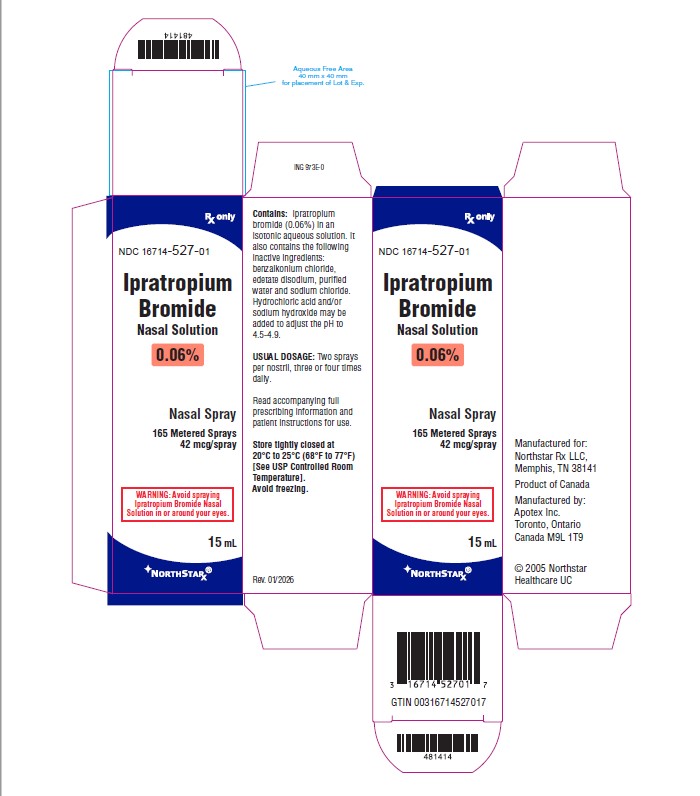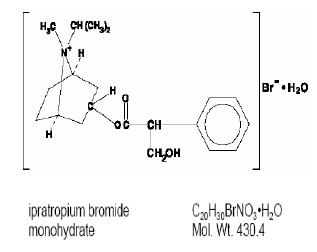 DRUG LABEL: Ipratropium Bromide
NDC: 16714-527 | Form: SPRAY, METERED
Manufacturer: NORTHSTAR RX LLC
Category: prescription | Type: HUMAN PRESCRIPTION DRUG LABEL
Date: 20260227

ACTIVE INGREDIENTS: IPRATROPIUM BROMIDE 42 ug/1 1
INACTIVE INGREDIENTS: BENZALKONIUM CHLORIDE; EDETATE DISODIUM; WATER; SODIUM CHLORIDE; HYDROCHLORIC ACID; SODIUM HYDROXIDE

IPRATROPIUM BROMIDE NASAL SOLUTION, 0.06%Nasal Spray Rx Only

DESCRIPTION

The active ingredient in ipratropium bromide nasal solution is ipratropium bromide monohydrate. It is an anticholinergic agent chemically described as 8-azoniabicyclo (3.2.1) octane, 3-(3-hydroxy-1-oxo-2-phenylpropoxy)-8-methyl-8-(1-methylethyl)-, bromide monohydrate (endo, syn)-, (+)-: a synthetic quaternary ammonium compound, chemically related to atropine. Its structural formula is:

Ipratropium bromide is a white to off-white crystalline substance. It is freely soluble in lower alcohols and water, existing in an ionized state in aqueous solutions, and relatively insoluble in non-polar media.

Ipratropium bromide nasal solution, 0.06% is a metered-dose, manual pump spray unit which delivers 42 mcg ipratropium bromide (on an anhydrous basis) per spray (70 mcL) in an isotonic, aqueous solution. It also contains the following inactive ingredients: benzalkonium chloride, edetate disodium, purified water and sodium chloride. Hydrochloric acid and/or sodium hydroxide may be added to adjust the pH to 4.5 to 4.9. Each bottle contains 165 sprays.

CLINICAL PHARMACOLOGY

Mechanism of Action

Ipratropium bromide is an anticholinergic (parasympatholytic) agent which, based on animal studies, appears to inhibit vagally-mediated reflexes by antagonizing the action of acetylcholine, the transmitter agent released at the neuromuscular junctions in the lung. In humans, ipratropium bromide has anti-secretory properties and, when applied locally, inhibits secretions from the serous and seromucous glands lining the nasal mucosa. Ipratropium bromide is a quaternary amine that minimally crosses the nasal and gastrointestinal membranes and the blood-brain barrier, resulting in a reduction of the systemic anticholinergic effects (e.g., neurologic, ophthalmic, cardiovascular, and gastrointestinal effects) that are seen with tertiary anticholinergic amines.

Pharmacokinetics

Absorption

Ipratropium bromide is poorly absorbed into the systemic circulation following oral administration (2 to 3%). Less than 20% of an 84 mcg per nostril dose was absorbed from the nasal mucosa of normal volunteers, induced-cold adult volunteers, naturally acquired common cold pediatric patients, or perennial rhinitis adult patients.

Distribution

Ipratropium bromide is minimally bound (0 to 9% in vitro) to plasma albumin and α1-acid glycoprotein. Its blood/plasma concentration ratio was estimated to be about 0.89. Studies in rats have shown that ipratropium bromide does not penetrate the blood-brain barrier.

Metabolism

Ipratropium bromide is partially metabolized to ester hydrolysis products, tropic acid and tropane. These metabolites appear to be inactive based on in vitro receptor affinity studies using rat brain tissue homogenates.

Elimination

After intravenous administration of 2 mg ipratropium bromide to 10 healthy volunteers, the terminal half-life of ipratropium bromide was approximately 1.6 hours. The total body clearance and renal clearance were estimated to be 2,505 and 1,019 mL/min, respectively. The amount of the total dose excreted unchanged in the urine (Ae) within 24 hours was approximately one-half of the administered dose.

Pediatrics

Following administration of 84 mcg of ipratropium bromide per nostril three times a day in patients 5 to 18 years old (n=42) with a naturally acquired common cold, the mean amount of the total dose excreted unchanged in the urine of 7.8% was comparable to 84 mcg per nostril four times a day in an adult induced common cold population (n=22) of 7.3 to 8.1%. Plasma ipratropium concentrations were relatively low (ranging from undetectable up to 0.62 ng/mL). No correlation of the amount of the total dose excreted unchanged in the urine (Ae) with age or gender was observed in the pediatric population.

Special Populations

Gender does not appear to influence the absorption or excretion of nasally administered ipratropium bromide. The pharmacokinetics of ipratropium bromide have not been studied in patients with hepatic or renal insufficiency or in the elderly.

Drug-Drug Interactions

No specific pharmacokinetic studies were conducted to evaluate potential drug-drug interactions.

Pharmacodynamics

In two single-dose trials (n=17), doses up to 336 mcg of ipratropium bromide did not significantly affect pupillary diameter, heart rate, or systolic/diastolic blood pressure. Similarly, ipratropium bromide nasal solution, 0.06% in adult patients (n=22) with induced-colds (84 mcg/nostril four times a day) and in pediatric patients (n=45) with naturally acquired common cold (84 mcg/nostril three times a day) had no significant effects on pupillary diameter, heart rate, or systolic/diastolic blood pressure.

Controlled clinical trials demonstrated that intranasal fluorocarbon-propelled ipratropium bromide does not alter physiologic nasal functions (e.g., sense of smell, ciliary beat frequency, mucociliary clearance, or the air conditioning capacity of the nose).

Clinical Trials

The clinical trials for ipratropium bromide nasal solution, 0.06% were conducted in patients with rhinorrhea associated with naturally occurring common colds. In two controlled four day comparisons of ipratropium bromide nasal solution, 0.06% (84 mcg per nostril, administered three or four times daily; n=352) with its vehicle (n=351), there was a statistically significant reduction of rhinorrhea, as measured by both nasal discharge weight and the patients’ subjective assessment of severity of rhinorrhea using a visual analog scale. These significant differences were evident within one hour following dosing. There was no effect of ipratropium bromide nasal solution, 0.06% on degree of nasal congestion or sneezing. The response to ipratropium bromide nasal solution, 0.06% did not appear to be affected by age or gender. No controlled clinical trials directly compared the efficacy of three times daily versus four times daily treatment.

One clinical trial was conducted with ipratropium bromide nasal solution, 0.06% administered four times daily for three weeks, in 218 patients with rhinorrhea associated with Seasonal Allergic Rhinitis (SAR), compared to its vehicle in 211 patients. Patients in this trial were adults and adolescents 12 years of age and above. Ipratropium bromide nasal solution, 0.06% was significantly more effective in reducing the severity and duration of rhinorrhea over the three weeks of the study, as measured by daily patient symptom scores. There was no difference between treatment groups in the effect on nasal congestion, sneezing or itching eyes.

INDICATIONS AND USAGE

Ipratropium bromide nasal solution, 0.06% is indicated for the symptomatic relief of rhinorrhea associated with the common cold or seasonal allergic rhinitis for adults and children age 5 years and older. Ipratropium bromide nasal solution, 0.06% does not relieve nasal congestion or sneezing associated with the common cold or seasonal allergic rhinitis.

The safety and effectiveness of the use of ipratropium bromide nasal solution, 0.06% beyond four days in patients with the common cold or beyond three weeks in patients with seasonal allergic rhinitis has not been established.

CONTRAINDICATIONS

Ipratropium bromide nasal solution, 0.06% is contraindicated in patients with a history of hypersensitivity to atropine or its derivatives, or to any of the other ingredients.

WARNINGS

Immediate hypersensitivity reactions may occur after administration of ipratropium bromide, as demonstrated by urticaria, angioedema, rash, bronchospasm, anaphylaxis, and oropharyngeal edema. If such a reaction occurs, therapy with ipratropium bromide nasal solution 0.06% should be stopped at once and alternative treatment should be considered.

PRECAUTIONS

General

1. Effects Seen with Anticholinergic Drugs: Ipratropium bromide nasal solution, 0.06% should be used with caution in patients with narrow-angle glaucoma, prostatic hyperplasia, or bladder neck obstruction, particularly if they are receiving an anticholinergic by another route.
2. Use in Hepatic or Renal Disease: Ipratropium bromide nasal solution, 0.06% has not been studied in patients with hepatic or renal insufficiency. It should be used with caution in those patient populations.

Information for Patients

Patients should be advised that temporary blurring of vision, precipitation or worsening of narrow-angle glaucoma, mydriasis, increased intraocular pressure, acute eye pain or discomfort, visual halos or colored images in association with red eyes from conjunctival and corneal congestion may result if ipratropium bromide nasal solution, 0.06% comes into direct contact with the eyes. Patients should be instructed to avoid spraying ipratropium bromide nasal solution, 0.06% in or around their eyes. Patients who experience eye pain, blurred vision, excessive nasal dryness or episodes of nasal bleeding should be instructed to contact their doctor. To ensure proper dosing, patients should be advised not to alter the size of the nasal spray opening. Patients should be reminded to carefully read and follow the accompanying Patient's Instructions for Use.

Since dizziness, accommodation disorder, mydriasis, and blurred vision may occur with use of ipratropium bromide nasal solution, 0.06%, patients should be cautioned about engaging in activities requiring balance and visual acuity such as driving a car or operating appliances, machinery, etc.

Drug Interactions

No controlled clinical trials were conducted to investigate potential drug-drug interactions. There is potential for an additive interaction with other concomitantly administered medications with anticholinergic properties, including ipratropium bromide for oral inhalation.

Carcinogenesis, Mutagenesis, Impairment of Fertility

Two-year oral carcinogenicity studies in rats and mice have revealed no carcinogenic activity at doses up to 6 mg/kg. This dose corresponds in rats and mice to approximately 70 and 35 times the maximum recommended daily intranasal dose in adults, respectively, and approximately 35 and 15 times the maximum recommended daily intranasal dose in children, respectively, on a mg/m^2 basis. Results of various mutagenicity studies (Ames test, mouse dominant lethal test, mouse micronucleus test, and chromosome aberration of bone marrow in Chinese hamsters) were negative.

Fertility of male or female rats at oral doses up to 50 mg/kg (approximately 600 times the maximum recommended daily intranasal dose in adults on a mg/m^2 basis) was unaffected by ipratropium bromide administration. At an oral dose of 500 mg/kg (approximately 6,000 times the maximum recommended daily intranasal dose in adults on a mg/m^2 basis), ipratropium bromide produced a decrease in the conception rate.

Pregnancy

Teratogenic Effects

Pregnancy Category B.

There are no adequate and well-controlled studies for ipratropium bromide nasal solution, 0.06% in pregnant women. Because animal reproduction studies are not always predictive of human response, ipratropium bromide nasal solution, 0.06% should be used during pregnancy only if clearly needed.

Oral reproduction studies were performed at doses of 10 mg/kg in mice, 1,000 mg/kg in rats and 125 mg/kg in rabbits. These doses correspond, in each species, respectively, to approximately 60, 12,000, and 3,000 times the maximum recommended daily intranasal dose (MRDID) in adults on a mg/m^2 basis. Inhalation reproduction studies were conducted in rats and rabbits at doses of 1.5 and 1.8 mg/kg, respectively, (approximately 20 and 45 times, respectively, the MRDID in adults on a mg/m^2 basis). These studies demonstrated no evidence of teratogenic effects as a result of ipratropium bromide. At oral doses 90 mg/kg and above in rats (approximately 1,100 times the MRDID in adults on a mg/m^2 basis) embryotoxicity was observed as increased resorption. This effect is not considered relevant to human use due to the large doses at which it was observed and the difference in route of administration.

Labor and Delivery

The effect of ipratropium bromide on labor and delivery is unknown.

Nursing Mothers

It is known that some ipratropium bromide is systemically absorbed following nasal administration; however the portion which may be excreted in human milk is unknown. Because lipid-insoluble quaternary cations pass into breast milk, caution should be exercised when ipratropium bromide nasal solution, 0.06% is administered to a nursing mother.

Pediatric Use

The safety of ipratropium bromide nasal solution, 0.06% at a dose of two sprays (84 mcg) per nostril three times a day (total dose 504 mcg/day) for two to four days has been demonstrated in two clinical trials involving 362 pediatric patients 5 to 11 years of age with naturally acquired common colds. In this pediatric population ipratropium bromide nasal solution, 0.06% had an adverse event profile similar to that observed in adolescent and adult patients. When ipratropium bromide nasal solution, 0.06% was concomitantly administered with an oral decongestant (pseudoephedrine HCI) in 122 children ages 5 to 12 years, and concomitantly administered with an oral decongestant/antihistamine combination (pseudoephedrine HCI/chlorpheniramine maleate) in 123 children ages 5 to 12 years, adverse event profiles were similar to ipratropium bromide nasal solution, 0.06% alone. The safety of ipratropium bromide nasal solution, 0.06% at a dose of two sprays (84 mcg) per nostril four times a day (total dose 672 mcg/day) for three weeks in pediatric seasonal allergic rhinitis patients down to 5 years is based upon the safety demonstrated in the pediatric common cold trials and the trial in adult and adolescent patients 12 to 75 years of age with seasonal allergic rhinitis. The effectiveness of ipratropium bromide nasal solution, 0.06% for the treatment of rhinorrhea associated with the common cold and seasonal allergic rhinitis in this pediatric age group is based on extrapolation of the demonstrated efficacy of ipratropium bromide nasal solution, 0.06% in adolescents and adults with the conditions and the likelihood that the disease course, pathophysiology, and the drug’s effects are substantially similar to that of adults. The recommended dose for common cold for the pediatric population is based on cross-study comparisons of the efficacy of ipratropium bromide nasal solution, 0.06% in adult and pediatric patients and on its safety profile in both adults and pediatric common cold patients. The recommended dose for seasonal allergic rhinitis for the pediatric population down to 5 years is based upon the efficacy and safety of ipratropium bromide nasal solution, 0.06% in adults and adolescents 12 years of age and above with seasonal allergic rhinitis and the safety profile of this dose in both adult and pediatric common cold patients. The safety and effectiveness of ipratropium bromide nasal solution, 0.06% in pediatric patients under 5 years of age have not been established.

ADVERSE REACTIONS

Adverse reaction information on ipratropium bromide nasal solution, 0.06% in patients with the common cold was derived from two multicenter, vehicle-controlled clinical trials involving 1,276 patients (195 patients on ipratropium bromide nasal solution, 0.03%, 352 patients on ipratropium bromide nasal solution, 0.06%, 189 patients on ipratropium bromide nasal spray, 0.12%, 351 patients on vehicle and 189 patients receiving no treatment).

Table 1 shows adverse events reported for patients who received ipratropium bromide nasal solution, 0.06% at the recommended dose of 84 mcg per nostril, or vehicle, administered three or four times daily, where the incidence is 1% or greater in the ipratropium bromide group and higher in the ipratropium bromide group than in the vehicle group.

Table 1 % of Patients with Common Cold Reporting Events^1
 | Ipratropium Bromide) Nasal Solution 0.06% | Vehicle Control
No. of Patients | 352 | 351
Epistaxis^2 | 8.2% | 2.3%
Nasal Dryness | 4.8% | 2.8%
Dry Mouth/Throat | 1.4% | 0.3%
Nasal Congestion | 1.1% | 0.0%
^1 This table includes adverse events for which the incidence was 1% or greater in the ipratropium bromide group and higher in the ipratropium bromide group than in the vehicle group.
^2 Epistaxis reported by 5.4% of ipratropium bromide patients and 1.4% of vehicle patients, blood-tinged nasal mucus by 2.8% of ipratropium bromide patients and 0.9% of vehicle patients.

Ipratropium bromide nasal solution, 0.06% was well tolerated by most patients. The most frequently reported adverse events were transient episodes of nasal dryness or epistaxis. The majority of these adverse events (96%) were mild or moderate in nature, none was considered serious, and none resulted in hospitalization. No patient required treatment for nasal dryness, and only three patients (<1%) required treatment for epistaxis, which consisted of local application of pressure or a moisturizing agent (e.g., petroleum jelly). No patient receiving ipratropium bromide nasal solution, 0.06% was discontinued from the trial due to either nasal dryness or bleeding.

Adverse events reported by less than 1% of the patients receiving ipratropium bromide nasal solution, 0.06% during the controlled clinical trials that are potentially related to ipratropium bromide's local effects or systemic anticholinergic effects include: taste perversion, nasal burning, conjunctivitis, coughing, dizziness, hoarseness, palpitation, pharyngitis, tachycardia, thirst, tinnitus, and blurred vision. No controlled trial was conducted to address the relative incidence of adverse events for three times daily versus four times daily therapy.

Nasal adverse events seen in the clinical trial with seasonal allergic rhinitis (SAR) patients (see Table 2) were similar to those seen in the common cold trials. Additional events were reported at a higher rate in the SAR trial due in part to the longer duration of the trial and the inclusion of Upper Respiratory Tract Infection (URI) as an adverse event. In common cold trials, URI was the disease under study and not an adverse event.

Table 2 % of Patients with SAR Reporting Events^1
 | Ipratropium Bromide) Nasal Solution 0.06% | Vehicle Control
No. of Patients | 218 | 211
Epistaxis^2 | 6.0% | 3.3%
Pharyngitis | 5.0% | 3.8%
URI | 5.0% | 3.3%
Nasal Dryness | 4.6% | 0.9%
Headache | 4.1% | 0.5%
Dry Mouth/Throat | 4.1% | 0.0%
Taste Perversion | 3.7% | 1.4%
Sinusitis | 2.8% | 2.8%
Pain | 1.8% | 0.9%
Diarrhea | 1.8% | 0.5%
^1 This table includes adverse events for which the incidence was 1% or greater in the ipratropium bromide group and higher in the ipratropium bromide group than in the vehicle group.
^2 Epistaxis reported by 3.7% of ipratropium bromide patients and 2.4% of vehicle patients, blood-tinged nasal mucus by 2.3% of ipratropium bromide patients and 1.9% of vehicle patients.

There were no reports of allergic-type reactions in the controlled clinical common cold and SAR trials.

Post-Marketing Experience

Allergic-type reactions such as skin rash, angioedema, including that of the throat, tongue, lips and face, generalized urticaria (including giant urticaria), laryngospasm, and anaphylactic reactions have been reported with ipratropium bromide nasal solution, 0.06% and for other ipratropium bromide containing products, with positive rechallenge in some cases.

Additional side effects identified from the published literature and/or post-marketing surveillance on the use of ipratropium bromide containing products (singly or in combination with albuterol), include: urinary retention, prostatic disorders, mydriasis, cases of precipitation or worsening of narrow-angle glaucoma, acute eye pain, ocular irritation wheezing, dryness of the oropharynx, , tachycardia, edema, gastrointestinal distress (diarrhea, nausea, vomiting), bowel obstruction, constipation, nasal discomfort, throat irritation, hypersensitivity, accommodation disorder, intraocular pressure increased, glaucoma, halo vision, conjunctival hyperaemia, corneal edema, heart rate increased, bronchospasm, pharyngeal edema, gastrointestinal motility disorder, mouth edema, stomatitis, and pruritus.

After oral inhalation of ipratropium bromide in patients suffering from COPD/Asthma supraventricular tachycardia and atrial fibrillation have been reported.

OVERDOSAGE

Acute overdosage by intranasal administration is unlikely since ipratropium bromide is not well absorbed systemically after intranasal or oral administration. Following administration of a 20 mg oral dose (equivalent to ingesting more than two bottles of ipratropium bromide nasal solution, 0.06%) to 10 male volunteers, no change in heart rate or blood pressure was noted. Following a 2 mg intravenous infusion over 15 minutes to the same 10 male volunteers, plasma ipratropium concentrations of 22 to 45 ng/mL were observed (>100 times the concentrations observed following intranasal administration). Following intravenous infusion these 10 volunteers had a mean increase of heart rate of 50 bpm and less than 20 mmHg change in systolic or diastolic blood pressure at the time of peak ipratropium levels.

DOSAGE AND ADMINISTRATION

For Symptomatic Relief of Rhinorrhea Associated with the Common Cold

The recommended dose of ipratropium bromide nasal solution, 0.06% is two sprays (84 mcg) per nostril three or four times daily (total dose 504 to 672 mcg/day) in adults and children age 12 years and older. Optimum dosage varies with response of the individual patient. The recommended dose of ipratropium bromide nasal solution, 0.06% for children age 5 to11 years is two sprays (84 mcg) per nostril three times daily (total dose of 504 mcg/day).

The safety and effectiveness of the use of ipratropium bromide nasal solution, 0.06% beyond four days in patients with the common cold have not been established.

For Symptomatic Relief of Rhinorrhea Associated with Seasonal Allergic Rhinitis

The recommended dose of ipratropium bromide nasal solution, 0.06% is two sprays (84 mcg) per nostril four times daily (total dose 672 mcg/day) in adults and children age 5 years and older.

The safety and effectiveness of the use of ipratropium bromide nasal solution, 0.06% beyond three weeks in patients with seasonal allergic rhinitis have not been established.

Initial pump priming requires seven sprays of the pump. If used regularly as recommended, no further priming is required. If not used for more than 24 hours, the pump will require two sprays, or if not used for more than seven days, the pump will require seven sprays to reprime. Avoid spraying into eyes.

HOW SUPPLIED

Ipratropium Bromide Nasal Solution, 0.06% is supplied in a white high density polyethylene (HDPE) bottle fitted with a metered nasal spray pump, a green safety clip to prevent accidental discharge of the spray, and a clear plastic dust cap (NDC 16714-527-01). It contains 16.6 g of product formulation, 165 sprays, each delivering 42 mcg of ipratropium bromide per spray (70 mcL), or 10 days of therapy at the maximum recommended dose (two sprays per nostril four times a day).

STORAGE AND HANDLING

Store tightly closed at 20° to 25°C (68° to 77°F) [See USP Controlled Room Temperature]. Avoid freezing. Keep out of reach of children. Do not spray in the eyes.

Address medical inquiries to Northstar Rx LLCat 1-800-206-7821

Patients should be reminded to read and follow the accompanying Patient's Instructions for Use, which should be dispensed with the product.

Manufactured for: | Manufactured by:
Northstar Rx LLC | Apotex Inc.
Memphis, TN 38141 | Toronto, Ontario
 | Canada M9L 1T9

December 2021

Patients Instructions for Use

Ipratropium Bromide Nasal Solution, 0.06%

Nasal spray

(ip" ra troe' pee um broe' mide)

Rx Only

Read complete instructions carefully before using.

In order to ensure proper dosing, do not attempt to change the size of the spray opening.

Ipratropium Bromide Nasal Solution, 0.06% is indicated for the symptomatic relief of rhinorrhea (runny nose) associated with the common cold or seasonal allergic rhinitis for adults and children age 5 years and older. Ipratropium Bromide Nasal Solution, 0.06% does not relieve nasal congestion or sneezing associated with the common cold or seasonal allergic rhinitis. Do not use Ipratropium Bromide Nasal Solution, 0.06% for longer than four days for a common cold or three weeks for seasonal allergic rhinitis unless instructed by your physician.

Read complete instructions carefully and use only as directed.

To Use

1. Remove the clear plastic dust cap and the green safety clip from the nasal spray pump (Figure 1). The safety clip prevents the accidental discharge of the spray in your pocket or purse.
  Figure 1
2. The nasal spray pump must be primed before Ipratropium Bromide Nasal Solution, 0.06% is used for the first time. To prime the pump, hold the bottle with your thumb at the base and your index and middle fingers on the white shoulder area. Make sure the bottle points upright and away from your eyes. Press your thumb firmly and quickly against the bottle seven times (Figure 2). The pump is now primed and can be used. Your pump should not have to be reprimed unless you have not used the medication for more than 24 hours; repriming the pump will only require two sprays. If you have not used your nasal spray for more than seven days, repriming the pump will require seven sprays.
  Figure 2
3. Before using Ipratropium Bromide Nasal Solution, 0.06%, blow your nose gently to clear your nostrils if necessary.
4. Close one nostril by gently placing your finger against the side of your nose, tilt your head slightly forward and, keeping the bottle upright, insert the nasal tip into the other nostril (Figure 3). Point the tip toward the back and outer side of the nose.
  Figure 3
5. Press firmly and quickly upwards with the thumb at the base while holding the white shoulder portion of the pump between your index and middle fingers. Following each spray, sniff deeply and breathe out through your mouth.
6. After spraying the nostril and removing the unit, tilt your head backwards for a few seconds to let the spray spread over the back of the nose.
7. Repeat steps 4 through 6 in the same nostril.
8. Repeat steps 4 through 7 in the other nostril (i.e., two sprays per nostril).
9. Replace the clear plastic dust cap and safety clip.
10. At some time before the medication is completely used up, you should consult your physician or pharmacist to determine whether a refill is needed. You should not take extra doses or stop using Ipratropium Bromide Nasal Solution, 0.06% without consulting your physician.

To Clean

If the nasal tip becomes clogged, remove the clear plastic dust cap and safety clip. Hold the nasal tip under running, warm tap water (Figure 4) for about a minute. Dry the nasal tip, reprime the nasal spray pump (step 2 above), and replace the plastic dust cap and safety clip.

Figure 4

Caution

Ipratropium Bromide Nasal Solution, 0.06% is intended to relieve your rhinorrhea (runny nose) with regular use. It is therefore important that you use Ipratropium Bromide Nasal Solution, 0.06% as prescribed by your physician. For most patients, some improvement in runny nose is apparent following the first dose of treatment with Ipratropium Bromide Nasal Solution, 0.06%. Do not use Ipratropium Bromide Nasal Solution, 0.06% for longer than four days for your cold or three weeks for seasonal allergic rhinitis unless instructed by your physician.

Do not spray Ipratropium Bromide Nasal Solution, 0.06% in your eyes. Should this occur, immediately flush your eye with cool tap water for several minutes. If you accidentally spray Ipratropium Bromide Nasal Solution, 0.06% in your eyes, you may experience a temporary blurring of vision, visual halos or colored images in association with red eyes from conjunctival and corneal congestion, development or worsening of narrow-angle glaucoma, pupil dilation, or acute eye pain/discomfort, and increased sensitivity to light, which may last a few hours. Should acute eye pain or blurred vision occur, contact your doctor.

Should you experience excessive nasal dryness or episodes of nasal bleeding, contact your doctor.

If you have glaucoma or difficulty urinating due to an enlargement of the prostate, be sure to tell your physician prior to using Ipratropium Bromide Nasal Solution, 0.06%.

If you are pregnant or you are breast feeding your baby, be sure to tell your physician prior to using Ipratropium Bromide Nasal Solution, 0.06%.

Address medical inquiries to Northstar Rx LLC at 1-800-206-7821.

Storage

Store tightly closed at 20°to 25°C (68° to 77°F) [See USP Controlled Room Temperature]. Avoid freezing. Keep out of reach of children.

Manufactured for: | Manufactured by:
Northstar Rx LLC | Apotex Inc.
Memphis, TN 38141 | Toronto, Ontario
 | Canada M9L 1T9

December 2021

PRINCIPAL DISPLAY PANEL- 0.06% Bottle Label

Northstar Rx LLC NDC 16714-527-01

Ipratropium Bromide Nasal Solution

0.06%

Nasal Spray

165 Metered Sprays

42 mcg/spray

Rx Only

15 mL

PRINCIPAL DISPLAY PANEL- 0.06% Carton Label

Northstar Rx LLC NDC 16714-527-01

Ipratropium Bromide Nasal Solution

0.06%

Nasal Spray

165 Metered Sprays

42 mcg/spray

Rx Only

15 mL